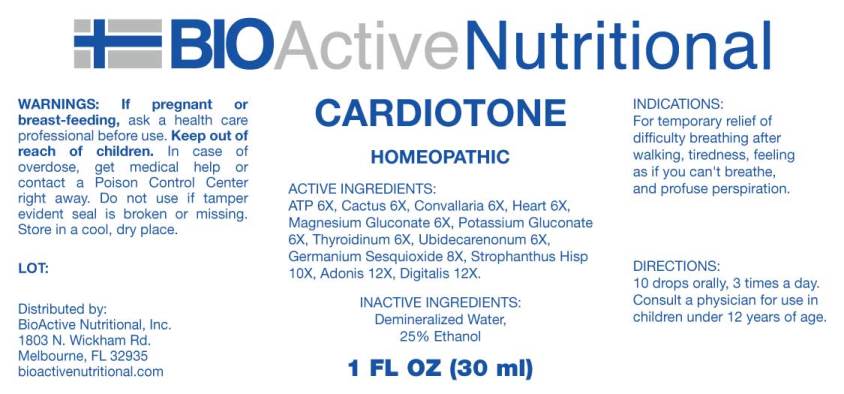 DRUG LABEL: Cardiotone
NDC: 43857-0512 | Form: LIQUID
Manufacturer: BioActive Nutritional, Inc.
Category: homeopathic | Type: HUMAN OTC DRUG LABEL
Date: 20240828

ACTIVE INGREDIENTS: ADENOSINE TRIPHOSPHATE DISODIUM 6 [hp_X]/1 mL; SELENICEREUS GRANDIFLORUS STEM 6 [hp_X]/1 mL; CONVALLARIA MAJALIS 6 [hp_X]/1 mL; PORK HEART 6 [hp_X]/1 mL; MAGNESIUM GLUCONATE 6 [hp_X]/1 mL; POTASSIUM GLUCONATE 6 [hp_X]/1 mL; THYROID 6 [hp_X]/1 mL; UBIDECARENONE 6 [hp_X]/1 mL; GERMANIUM SESQUIOXIDE 8 [hp_X]/1 mL; STROPHANTHUS HISPIDUS SEED 10 [hp_X]/1 mL; ADONIS VERNALIS WHOLE 12 [hp_X]/1 mL; DIGITALIS 12 [hp_X]/1 mL
INACTIVE INGREDIENTS: WATER; ALCOHOL

DRUG FACTS:

ACTIVE INGREDIENTS:

Adenosinum Triphosphoricum Dinatrum 6X, Cactus Grandiflorus 6X, Convallaria Majalis 6X, Heart (Suis) 6X, Magnesium Gluconate 6X, Potassium Gluconate 6X, Thyroidinum (Suis) 6X, Ubidecarenonum 6X, Germanium Sesquioxide 8X, Strophanthus Hispidus 10X, Adonis Vernalis 12X, Digitalis Purpurea 12X.

INDICATIONS:

For temporary relief of difficulty breathing after walking, tiredness, feeling as if you can't breathe, and profuse perspiration.

WARNINGS:

If pregnant or breast-feeding, ask a health care professional before use.

Keep out of reach of children. In case of overdose, get medical help or contact a Poison Control Center right away.

Do not use if tamper evident seal is broken or missing.

Store in a cool, dry place.

Keep out of reach of children. In case of overdose, get medical help or contact a Poison Control Center right away.

DIRECTIONS:

10 drops orally, 3 times a day. Consult a physician for use in children under 12 years of age.

INDICATIONS:

For temporary relief of difficulty breathing after walking, tiredness, feeling as if you can't breathe, and profuse perspiration.

INACTIVE INGREDIENTS:

Demineralized Water, 25% Ethanol

QUESTIONS:

Distributed by:
BioActive Nutritional, Inc.
1803 N. Wickham Rd.
Melbourne, FL 32935
bioactivenutritional.com

PACKAGE LABEL DISPLAY:

BIOActive Nutritional

CARDIOTONE

HOMEOPATHIC

1 FL OZ (30 ml)